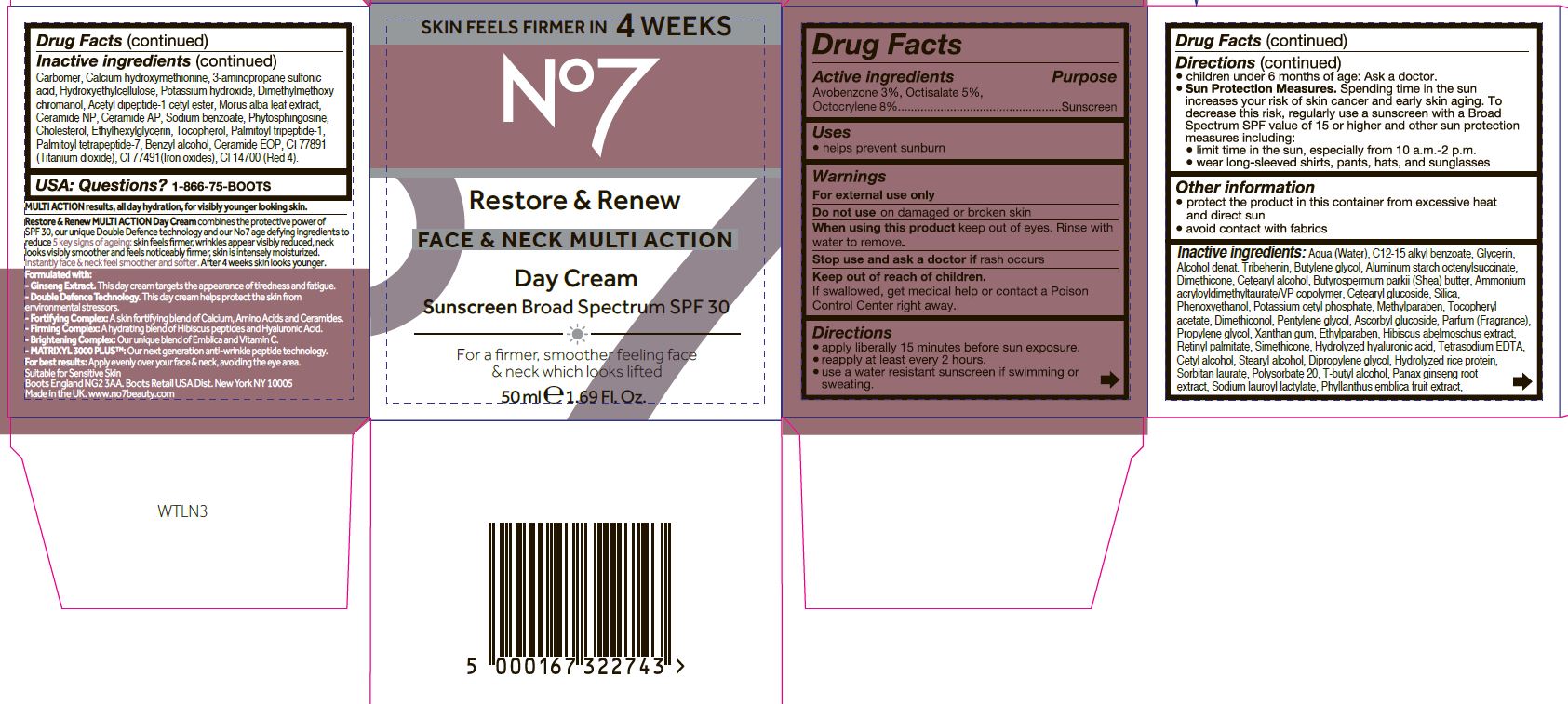 DRUG LABEL: No7Restore and Renew Face and Neck Multi Action Day Cream Sunscreen Broad Spectrum SPF 30
NDC: 11489-127 | Form: CREAM
Manufacturer: BCM Ltd
Category: otc | Type: HUMAN OTC DRUG LABEL
Date: 20230201

ACTIVE INGREDIENTS: AVOBENZONE 1.5 g/1 g; OCTOCRYLENE 4.0 g/1 g; OCTISALATE 2.5 g/1 g
INACTIVE INGREDIENTS: WATER; GLYCERIN; ALUMINUM STARCH OCTENYLSUCCINATE; CETEARYL GLUCOSIDE; DIMETHICONE; TRIBEHENIN; AMMONIUM ACRYLOYLDIMETHYLTAURATE/VP COPOLYMER; PHENOXYETHANOL; SHEA BUTTER; POTASSIUM CETYL PHOSPHATE; BUTYLENE GLYCOL; DIMETHICONOL (100000 CST); PROPYLENE GLYCOL; METHYLPARABEN; PENTYLENE GLYCOL; ETHYLPARABEN; DIPROPYLENE GLYCOL; SODIUM LAUROYL LACTYLATE; PHYLLANTHUS EMBLICA FRUIT; XANTHAN GUM; HYDROXYETHYL CELLULOSE (100 MPA.S AT 2%); PANAX GINSENG ROOT OIL; VITAMIN A PALMITATE; ASCORBYL GLUCOSIDE; EDETATE SODIUM; TERT-BUTYL ALCOHOL; DIMETHYLMETHOXY CHROMANOL; N-ACETYL DIPEPTIDE-1; POLYSORBATE 20; POTASSIUM HYDROXIDE; CARBOMER 940; MORUS ALBA LEAF; CERAMIDE 3; SODIUM BENZOATE; PHYTOSPHINGOSINE; CERAMIDE 6 II; CHOLESTEROL; ETHYLHEXYLGLYCERIN; TOCOPHEROL; CERAMIDE 1; TITANIUM DIOXIDE; BROWN IRON OXIDE; PALMITOYL TRIPEPTIDE-1; PALMITOYL TETRAPEPTIDE-7

No7 Restore and Renew Face and Neck Multi Action Day Cream Sunscreen Broad Spectrum SPF 30

Carton Active Ingredients Section

Active ingredients

Avobenzone 3%

Octisalate 5%

Octocrylene 8%

Uses

Uses - helps prevent sunburn

Warnings

For external use only

Do not use on damaged or broken skin

When using this product keep out of eyes. Rinse with water to remove.

Ask a doctor

Stop use and ask a doctor if rash occurs

Keep out of reach of children

If swallowed, get medical help or contact a Poison Control Center right away

Directions

Apply liberally 15 minutes before sun exposure

reapply at least every 2 hours

use a water resistant sunscreen if swimming or sweating

children under 6 months of age: Ask a doctor

Sun Protection Measures. Spending time in the sun increases your risk of skin cancer and early skin aging.

To decrease this risk, regularly use a sunscreen with a Broad Spectrum SPF value of 15 or higher and other sun protection measures including:

Limit time in the sun, especially from 10 a.m - 2 p.m.

wear long-sleeved shirts,pants,hats and sunglasses.

Storage

Other information

Protect the product in this container from excessive heat and direct sun

Avoid contact with fabrics

Inactive ingredients

Aqua(Water), Glycerin, C12-15 alkyl benzoate,Tribehenin, Alcohol denat, Dimethicone, Aluminum starch octenylsuccinate, Butylene glycol, Cetearyl alcohol, Cetearyl glucoside, Butyrospermum parkii(Shea)butter, Ammonium acryloydimethyltaurate/VP copolymer, Phenoxyethanol, Potassium cetyl phosphate, Methylparaben, Parfum(Fragrance), Dimethiconol, Pentylene glycol, Propylene glycol, Xanthan gum, Tocopheryl acetate, Ascorbyl glucoside, Ethylparaben, Hibiscus abelmoschus extract, Retinyl palmitate, Simethicone, Hydrolyzed hyaluronic acid, Dipropylene glycol, Hydrolyzed rice protein, Tetrasodium EDTA, Sorbitan laurate, T-butyl alcohol, Sodium lauroyl lactylate, Phyllanthus emblica fruit extract, Calcium hydroxymethionine, 3-aminopropane sulfonic acid, Hydroxyethylcellulose, Acetyl dipeptide-1 cetyl ester, Ceramide 3, Ceramide 6 11,

Panax ginseng root extract, Dimethylmethoxy chromanol, Carbomer, Potassium hydroxide, Polysorbate 20, Morus alba leaf extract, Silica, Sodium benzoate, Phytosphingsine, Cholesterol,Tocopherol, Ethylhexylglycerin, Palmitoyl tripeptide-1, Palmitoyl tetrapeptide-7, Ceramide 1, CI 77891(Titanium dioxide), CI 77491 (Iron oxides) CI 14700(Red 4)

Description

SKIN FEELS FIRMER IN 4 WEEKS

No7 Restore & Renew FACE & NECK MULTI ACTION Day Cream Sunscreen Broad Spectrum SPF 30

For a firmer, smoother feeling face & neck which looks lifted

50 ml e 1.69 Fl.Oz.

MULTI ACTION results, all day hydration, for visibly younger looking skin.

Restore & Renew MULTI ACTION Day Cream combines the protective power of SPF 30, our unique Double Defence technology and our No7 age defying ingredients to reduce 5 key signs of ageing: skin feels firmer, wrinkles appear visibly reduced, neck looks visibly smoother and feels noticeably firmer, skin is intensely moisturized. Instantly face & neck feel smoother and softer. After 4 weeks skin looks younger.

Formulated with:

- Ginseng Extract. This day cream targets the appearance of tiredness and fatigue.

- Double Defence Technology. This day cream helps protect the skin from environmental stressors.

- Fortifying Complex: A skin fortifying blend of Calcium, Amino Acids and Ceramides.

- Firming Complex: A hydrating blend of Hibiscus peptides and Hyaluronic Acid.

- Brightening Complex: Our unique blend of Emblica and Vitamin C.

- MATRIXYL 3000 PLUS: Our next generation anti-wrinkle peptide technology.

Suitable for Sensitive Skin

PATIENT COUNSELING INFORMATION

Boots England NG2 3AA. Boots Retail USA Dist. New York NY 10005

Made in the UK. www.No7beauty.com

Carton